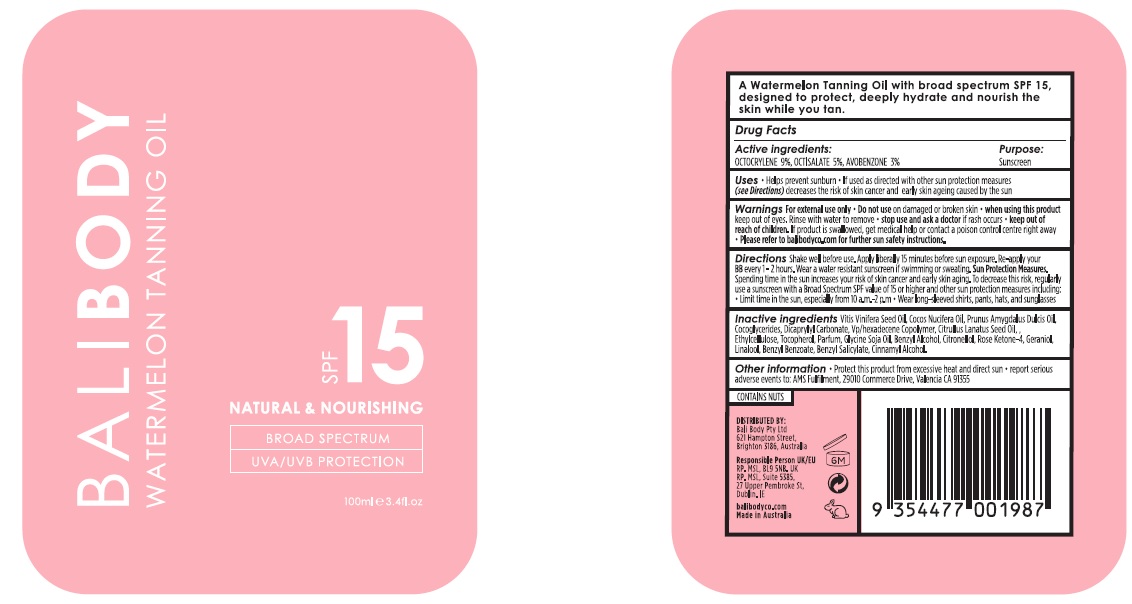 DRUG LABEL: Bali Body Watermelon Tanning Oil SPF 15
NDC: 70630-0035 | Form: OIL
Manufacturer: Bali Body Pty Ltd
Category: otc | Type: HUMAN OTC DRUG LABEL
Date: 20241103

ACTIVE INGREDIENTS: AVOBENZONE 30 mg/1 mL; OCTISALATE 50 mg/1 mL; OCTOCRYLENE 90 mg/1 mL
INACTIVE INGREDIENTS: VINYLPYRROLIDONE/HEXADECENE COPOLYMER; BENZYL ALCOHOL; GERANIOL; LINALOOL, (+/-)-; BENZYL SALICYLATE; BENZYL BENZOATE; SOYBEAN OIL; .BETA.-CITRONELLOL, (R)-; CINNAMYL ALCOHOL; TOCOPHEROL; ALMOND OIL; COCONUT OIL; DICAPRYLYL CARBONATE; WATERMELON SEED OIL; COCO-GLYCERIDES; ETHYLCELLULOSE, UNSPECIFIED; GRAPE SEED OIL

Bali Body Watermelon Tanning Oil SPF 15

Active ingredients:

Octocrylene 9%

Octisalate 5%

Avobenzone 3%

Purpose:

Sunsreen

Uses

- Helps prevent sunburn
- If used as directed with other sun protection measures (see Directions) decreases the risk of skin cancer and early skin ageing caused by the sun

Warnings

For external use only.

Do not use

on damaged or broken skin.

When using this product

keep out of eyes. Rinse with water to remove.

Stop use and ask a doctor

if rash occurs.

Keep out of reach of children.

If product is swallowed, get medical help or contact a poison control centre right away.

- Please refer to balibodyco.com for further sun safety instructions.

Directions

Shake well before use. Apply liberally 15 minutes before sun exposure. Re-apply your BB every 1-2 hours. Wear a water resistant sunscreen if swimming or sweating. Sun Protection Measures. Spending time in the sun increases your risk of skin cancer and early skin aging. To decrease this risk, regularly use a sunscreen with a Broad Spectrum SPF value of 15 or higher and other sun protection measures including:

- Limit time in the sun, especially from 10 a.m. - 2 p.m.
- Wear long-sleeved shirts, pants, hats, and sunglasses

Inactive ingredients

Vitis Vinifera Seed Oil, Cocos Nucifera Oil, Prunus Amygdalus Dulcis Oil, Cocoglycerides, Dicaprylyl Carbonate, Vp/hexadecene Copolymer, Citrullus Lanatus Seed Oil, Ethylcellulose, Tocopherol, Parfum, Glycine Soja Oil, Benzyl Alcohol, Citronellol, Rose Ketone-4, Geranol, Linalool, Benzyl Benzoate, Benzyl Salicylate, Cinnamyl Alcohol.

Other information

- Protect this product from excessive heat and direct sun
- Report serious adverse events to: AMS Fulfilment, 29010 Commerce Drive, Valencia CA 91355